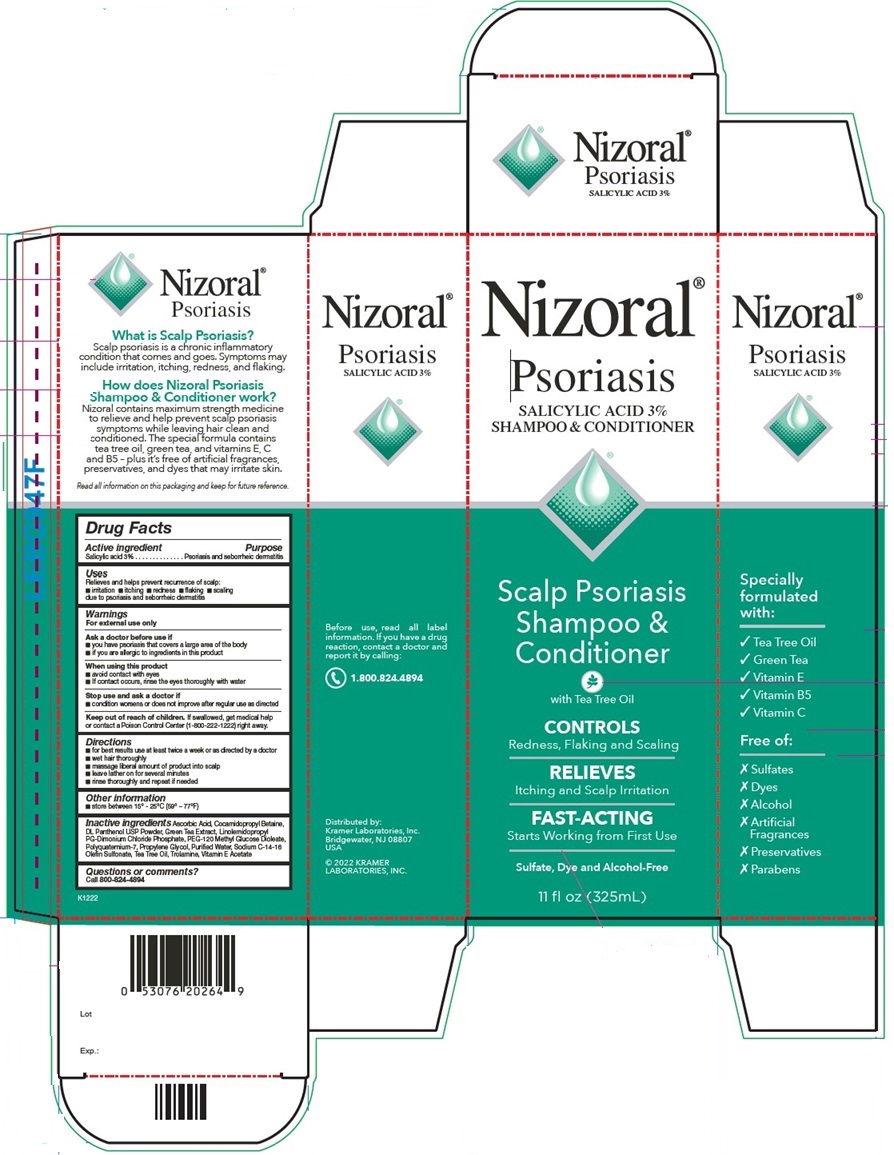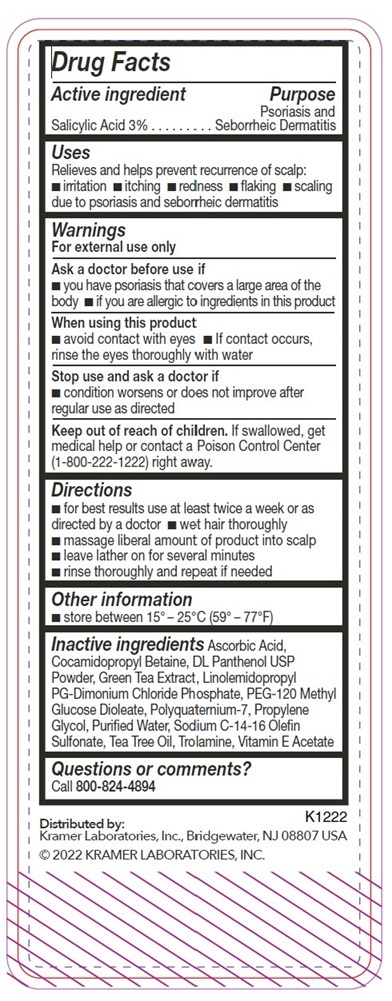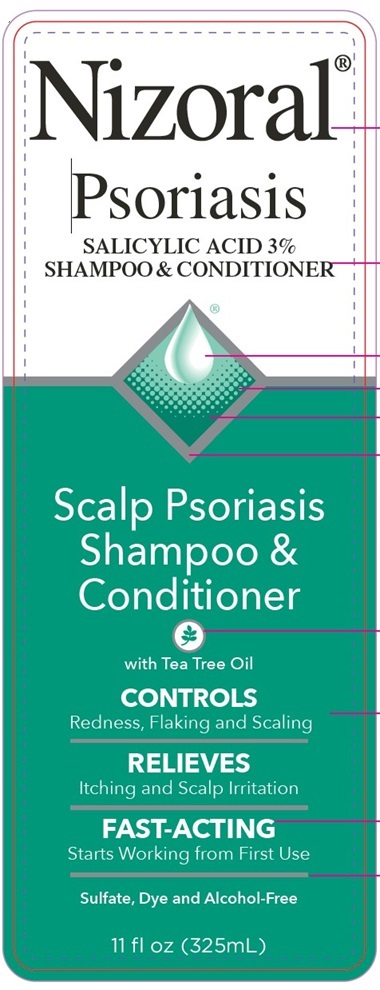 DRUG LABEL: Nizoral Psoriasis
NDC: 55505-202 | Form: SHAMPOO
Manufacturer: Kramer Laboratories
Category: otc | Type: HUMAN OTC DRUG LABEL
Date: 20251223

ACTIVE INGREDIENTS: Salicylic Acid 3 g/100 mL
INACTIVE INGREDIENTS: Water; Sodium C14-16 Olefin Sulfonate; Cocamidopropyl Betaine; Peg-120 Methyl Glucose Dioleate; Polyquaternium-7 (70/30 Acrylamide/Dadmac; 1600000 Mw); Trolamine; Panthenol; .Alpha.-Tocopherol Acetate; Tea Tree Oil; Green Tea Leaf; Ascorbic Acid

Drug Facts

ACTIVE INGREDIENT

Active ingredient | Purpose
Salicylic Acid 3% | Psoriasis and Seborrheic Dermatitis

Uses
Relieves and helps prevent recurrence of scalp:

- irritation
- itching
- redness
- flaking
- scaling due to psoriasis and seborrheic dermatitis

Warnings
For external use only

Ask a doctor before use if

- you have psoriasis that covers a large area of the body
- if you are allergic to ingredients in this product

When using this product

- avoid contact with eyes
- If contact occurs, rinse the eyes thoroughly with water

Stop use and ask a doctor if

- condition worsens or does not improve after regular use as directed

Keep out of reach of children. If swallowed, get medical help or contact a Poison Control Center (1-800-222-1222) right away.

Directions

- for best results use at least twice a week or as directed by a doctor
- wet hair thoroughly
- massage liberal amount of product into scalp
- leave lather on for several minutes
- rinse thoroughly and repeat if needed

Other information

- store between 20° – 25°C (68° – 77°F)

Inactive ingredients

Ascorbic Acid, Cocamidopropyl Betaine, DL Panthenol USP Powder, Green Tea Extract, Linolemidopropyl PG-Dimonium Chloride Phosphate, PEG-120 Methyl Glucose Dioleate, Polyquaternium-7, Propylene Glycol, Puried Water, Sodium C-14-16 Olefin Sulfonate, Tea Tree Oil, Trolamine, Vitamin E Acetate

Questions or comments?

Call 800-824-4894

Principal Display Panel

Nizoral®
Psoriasis
SALICYLIC ACID 3%
SHAMPOO & CONDITIONER
Scalp Psoriasis
Shampoo &
Conditioner
with Tea Tree Oil
CONTROLS
Redness, Flaking and Scaling
RELIEVES
Itching and Scalp Irritation
FAST-ACTING
Starts Working from First Use
Sulfate, Dye and Alcohol-Free
11 fl oz (325mL)
Specially formulated with:
✓ Tea Tree Oil
✓ Green Tea
✓ Vitamin E
✓ Vitamin B5
✓ Vitamin C
Free of:
X Sulfates
X Dyes
X Alcohol
X Artificial Fragrances
X Preservatives
X Parabens
What is Scalp Psoriasis?
Scalp psoriasis is a chronic inflammatory
condition that comes and goes. Symptoms may
include irritation, itching, redness, and flaking.
How does Nizoral Psoriasis
Shampoo & Conditioner work?
Nizoral contains maximum strength medicine
to relieve and help prevent scalp psoriasis
symptoms while leaving hair clean and
conditioned. The special formula contains
tea tree oil, green tea and vitamins E, C
and B5 - plus it's free of artificial fragrances,
preservatives, and dyes that may irritate skin.
Read all information on this packaging and keep for future reference.
Before use, read all label
information. If you have a drug
reaction, contact a doctor and
report it by calling:
1.800.824.4894
Distributed by:
Kramer Laboratories, Inc.
Bridgewater, NJ 08807
USA
© 2022 KRAMER
LABORATORIES, INC.
K1222

Nizoral®
Psoriasis
SALICYLIC ACID 3%
SHAMPOO & CONDITIONER
Scalp Psoriasis
Shampoo &
Conditioner
with Tea Tree Oil
CONTROLS
Redness, Flaking and Scaling
RELIEVES
Itching and Scalp Irritation
FAST-ACTING
Starts Working from First Use
Sulfate, Dye and Alcohol-Free
11 fl oz (325mL)